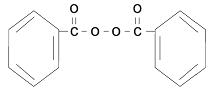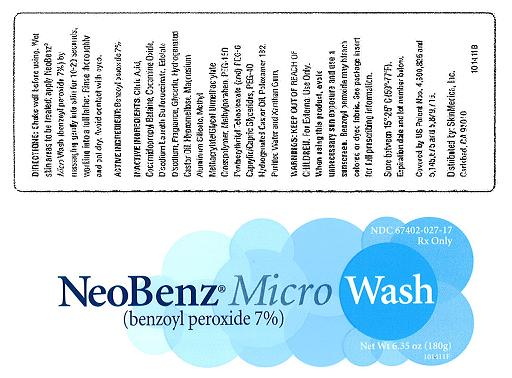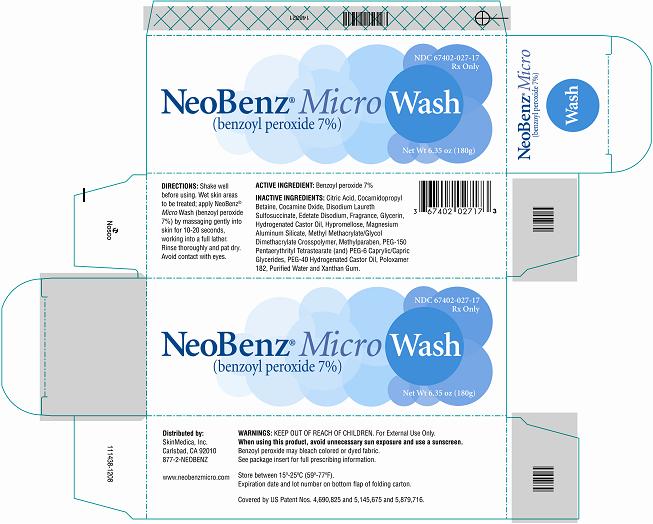 DRUG LABEL: NeoBenz(R) Micro
NDC: 67402-027 | Form: LOTION
Manufacturer: SkinMedica Pharmaceuticals, Inc., Carlsbad, CA 92010
Category: prescription | Type: HUMAN PRESCRIPTION DRUG LABEL
Date: 20090706

ACTIVE INGREDIENTS: BENZOYL PEROXIDE 70 mg/1 g

NeoBenz® Micro
(benzoyl peroxide cream)
NeoBenz® Micro SD
(benzoyl peroxide cream)
NeoBenz® Micro Wash
(benzoyl peroxide)
Rx ONLY.
FOR EXTERNAL USE ONLY.

I. DESCRIPTION

NeoBenz® Micro 3.5% and 5.5% creams, NeoBenz® Micro SD 5.5% single dose cream and NeoBenz® Micro Wash 7% are topical preparations containing benzoyl peroxide as the active ingredient incorporated into patented porous microspheres (MICROSPONGE®* delivery system) composed of methyl methacrylate/glycol dimethacrylate crosspolymer. This polymeric system has been shown to provide gradual release of active ingredient into the skin^1 and absorb natural skin oils^2. Ingredients for all cream and SD strengths include: water, glycerin, ethylhexyl palmitate, sorbitol, cetyl alcohol, glyceryl ditaurate, stealryl alcohol, magnesium aluminum silicate, methyl methacrylate/glycol dimethacrylate crosspolymer, silica, citric acid, xanthan gum, methylparaben, sodium citrate, propyIparaben, polyacrylamide, C13-14 isoparaffin, laureth-7, sodium lauryl sulfate. Ingredients for the Wash include citric acid, cocamidopropyl betaine, cocamine oxide, disodium laureth sulfosuccinate, edetate disodium, fragrance, glycerin, hydrogenated castor oil, hypromellose, magnesium aluminum silicate, methyl methacrylate/Glycol dimethacrylate crosspolymer, methylparaben, PEG-150 pentaerythrityl tetrastearate (and) PEG-6 caprylic/capric glycerides, PEG-40 hydrogenated castor oil, poloxamer 182, purified water and xanthan gum.
Benzoyl peroxide is an oxidizing agent that possesses antibacterial properties and is classified as a keratolytic. Benzoyl peroxide (C14H10O4) is represented by the following structure:

II. CLINICAL PHARMACOLOGY

The exact method of action of benzoyl peroxide in acne vulgaris is not known. Benzoyl peroxide is an antibacterial agent with demonstrated activity against Propionibacterium acnes. This action, combined with the mild keratolytic effect of benzoyl peroxide is believed to be responsible for its usefulness in acne. Benzoyl peroxide is absorbed by the skin where it is metabolized to benzoic acid and excreted as benzoate in the urine.

III. INDICATIONS AND USAGE

NeoBenz® Micro, NeoBenz® Micro SD and NeoBenz® Micro Wash are indicated for use in the topical treatment of mild to moderated acne vulgaris.

IV. CONTRAINDICATIONS

NeoBenz® Micro, NeoBenz® Micro SD and NeoBenz® Micro Wash should not be used in patients who have shown hypersensitivity to benzoyl peroxide or to any of the other ingredients in the products.

V. WARNINGS

When using this product, avoid unnecessary sun exposure and use a sunscreen.

VI. PRECAUTIONS

(SEE WARNINGS)
General– For external use only. Avoid contact with eyes and mucous membranes. If severe irritation develops, discontinue use and institute appropriate therapy.

PATIENT COUNSELING INFORMATION

Information for Patients: Avoid contact with eyes, eyelids, lips and mucous membranes. If accidental contact occurs, rinse with water. AVOID CONTACT WITH HAIR, FABRICS OR CARPETING AS BENZOYL PEROXIDE WILL CAUSE BLEACHING OR DISCOLORATION. If excessive irritation develops, discontinue use and consult your physician.

CARCINOGENESIS AND MUTAGENESIS AND IMPAIRMENT OF FERTILITY

Carcinogenesis, Mutagenesis, Impairment of Fertility: Based upon all available evidence, benzoyl peroxide is not considered to be a carcinogen. However, data from a study using mice known to be highly susceptible to cancer suggest that benzoyl peroxide acts as a tumor promoter. The clinical significance of the findings is not known.

PREGNANCY

Pregnancy: Category C - Animal reproduction studies have not been conducted with benzoyl peroxide. It is also not known whether benzoyl peroxide can cause fetal harm when administered to a pregnant woman or can affect reproduction capacity. Benzoyl peroxide should be used by a pregnant woman only if clearly needed.

NURSING MOTHERS

Nursing Mothers: It is not known whether this drug is excreted in human milk. Because many drugs are excreted in human milk, caution should be exercised when benzoyl peroxide is administered to a nursing woman.

PEDIATRIC USE

Pediatric Use: Safety and effectiveness in children below the age of 12 have not been established.

VII . ADVERSE REACTIONS

Allergic contact dermatitis and dryness have been reported with topical benzoyl peroxide therapy.

VIII. OVERDOSAGE

If excessive scaling, erythema or edema occurs, the use of these preparations should be discontinued. To hasten resolution of the adverse effects, cool compresses may be used. After symptoms and signs subside, a reduced dosage schedule may be cautiously tried if the reaction is judged to be due to excessive use and not allergenicity.

IX. DOSAGE AND ADMINISTRATION

NeoBenz® Micro, NeoBenz® Micro SD and NeoBenz® Micro Wash should be used once or twice daily on the affected areas. Frequency of use should be adjusted to obtain the desired clinical response. If you see medication or white residue on skin after application of NeoBenz® Micro or NeoBenz® Micro SD, you are applying too much. Gentle cleansing of the affected areas with a mild cleanser prior to application of NeoBenz® Micro or NeoBenz® Micro SD may be beneficial. Clinically visible improvement will normally occur by the third week if therapy. Maximum lesion reduction may be expected after approximately eight to twelve weeks for drug use. Continuing use of the drug us normally required to maintain a satisfactory clinical response.
NeoBenz® Micro: If applying to the entire face, apply a pea-sized amount of NeoBenz® Micro to one fingertip and dab onto cheeks, forehead and chin. Spread evenly onto entire face.
NeoBenz® Micro SD: Firmly squeeze applicator until seal between applicator and sponge has broken. Apply medication by rubbing sponge on small circular motions on affected areas. Dispose of each applicator after single use only.
NeoBenz® Micro Wash: Shake well before using. Wet skin areas to be treated; apply NeoBenz® Micro Wash by massaging gently into skin for 10-20 seconds, working into a full lather. Rinse thoroughly and pat dry.

X. HOW SUPPLIED

NeoBenz® Micro is supplied as follows:
SIZE: 45 gram tube
NDC NUMBER:
(3.5% benzoyl peroxide cream): 67402-020-45
(5.5% benzoyl peroxide cream): 67402-021-45
NeoBenz® Micro SD is supplied as follows:
SIZE: 1 box of thirty 0.5 gram applicators
NDC NUMBER:
(5.5% benzoyl peroxide cream): 67402-021-06
NeoBenz® Micro Wash is supplied as follows:
SIZE: 180 gram tottle
NDC NUMBER:
(benzoyl peroxide 7%): 67402-027-17

STORAGE AND HANDLING

Store between 15o - 25o C (59o - 77o F)

REFERENCES

1. Wester RC, Patel R, Nacht S, Leyden J, Melendres J, Maibach H. Controlled release of benzoyl peroxide from a porous microsphere polymeric system can reduce topical irritancy. J. Am. Acad. Dermatol. 1991;24; 720-726.
2. Meyer R. Rosen (ed.), Delivery System Handbook for Personal care and Cosmetic Products, 332-352 (2005).

Distributed by SkinMedica Pharmaceuticals, Inc., Carlsbad. CA 92010
Covered by Us Patents: 4,690,825; 5,145,675; 5,879,716; 6,007,364.
*MICROSPONGE® is a registered trademark of AMCOL Health and Beauty Solutions, Inc, a subsidiary of AMCOL International Corporation.
129008 December 2008
P7001-03